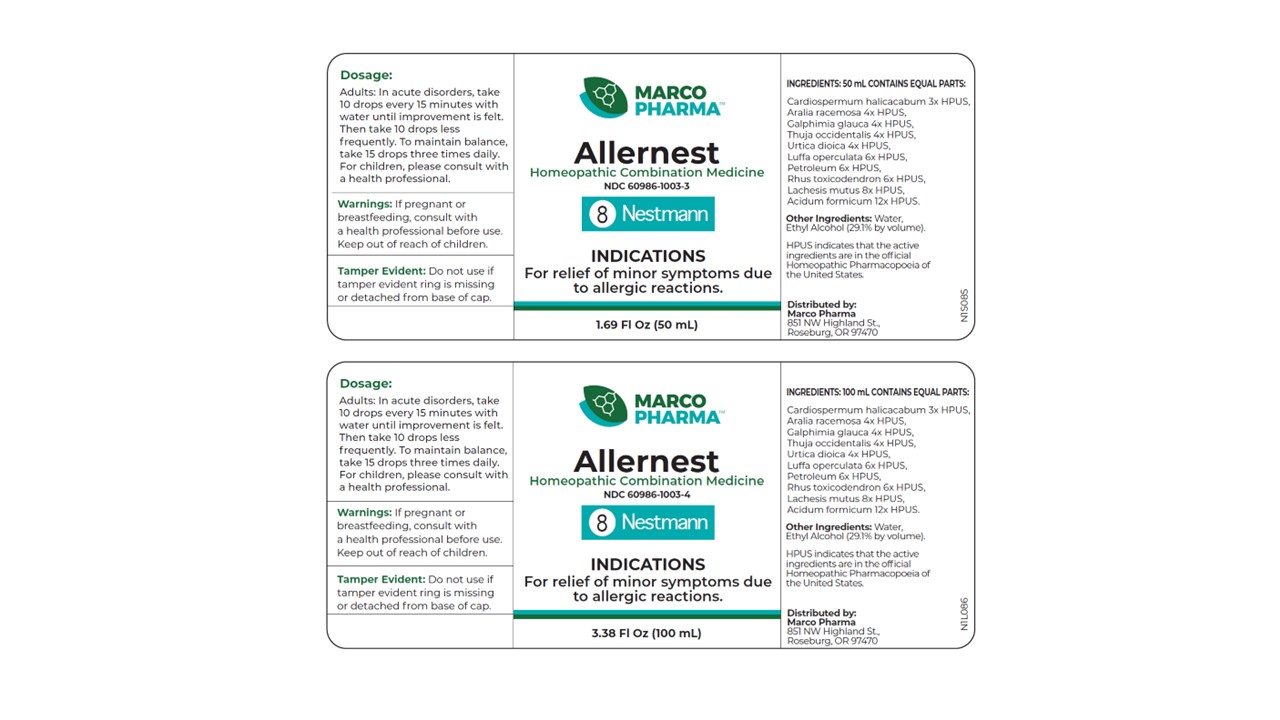 DRUG LABEL: Allernest
NDC: 60986-1003 | Form: LIQUID
Manufacturer: Marco Pharma International LLC.
Category: homeopathic | Type: HUMAN OTC DRUG LABEL
Date: 20260112

ACTIVE INGREDIENTS: FORMIC ACID 12 [hp_X]/1 mL; LACHESIS MUTA VENOM 8 [hp_X]/1 mL; LUFFA OPERCULATA FRUIT 6 [hp_X]/1 mL; KEROSENE 6 [hp_X]/1 mL; TOXICODENDRON PUBESCENS LEAF 6 [hp_X]/1 mL; ARALIA RACEMOSA ROOT 4 [hp_X]/1 mL; GALPHIMIA GLAUCA FLOWERING TOP 4 [hp_X]/1 mL; THUJA OCCIDENTALIS LEAFY TWIG 4 [hp_X]/1 mL; URTICA DIOICA 4 [hp_X]/1 mL; CARDIOSPERMUM HALICACABUM FLOWERING TOP 3 [hp_X]/1 mL
INACTIVE INGREDIENTS: WATER; ALCOHOL

Drug Facts

Active Ingredients

Formic acid 12xHPUS

Bushmaster Viper 8xHPUS

Purging luffa 6xHPUS

Kerosene 6xHPUS

Poison Ivy 6xHPUS

Spikenard 4xHPUS

Thryallis 4xHPUS

White cedar 4xHPUS

Stinging nettle 4xHPUS

Balloon vine 3xHPUS

The letters HPUS indicates that the components in this product are officially monographed in the Homeopathic Pharmacopoeia of United Sates.

Purpose

Relief of mild allergic reactions.

Keep out of reach of children.

Suggested use

Adults: in acute disorders, take 10 drops every 15 minutes on the tongue or with water until improvement if felt, then take 10 drops less frequently. To maintain balance, take 15 drops three times daily. Children receive 1/2 of the adult amount.

Warnings

If pregnant or breast-feeding, consult a health professional before use.

DOSAGE AND ADMINISTRATION

(Read Suggested Use Section)

Inactive Ingredients

Ethyl Alcohol (29.1% by vol.) and Water